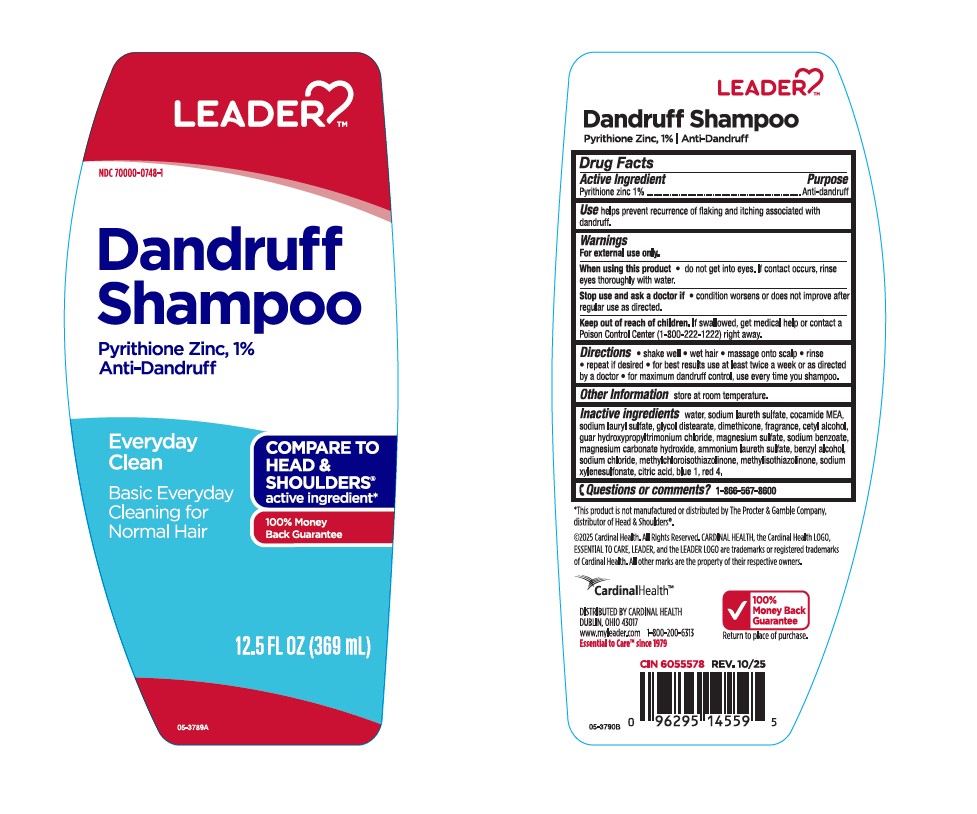 DRUG LABEL: Dandruff
NDC: 70000-0748 | Form: SHAMPOO
Manufacturer: CARDINAL HEALTH 110, LLC. DBA LEADER
Category: otc | Type: HUMAN OTC DRUG LABEL
Date: 20251124

ACTIVE INGREDIENTS: Pyrithione Zinc 10 mg/1 mL
INACTIVE INGREDIENTS: Water; Sodium Laureth-3 Sulfate; Coco Monoethanolamide; Sodium Lauryl Sulfate; Glycol Distearate; Dimethicone; Cetyl Alcohol; Guar Hydroxypropyltrimonium Chloride (1.7 Substituents Per Saccharide); Magnesium Sulfate, Unspecified Form; Sodium Benzoate; Magnesium Carbonate Hydroxide; Ammonium Laureth-5 Sulfate; Benzyl Alcohol; Sodium Chloride; Methylchloroisothiazolinone; Methylisothiazolinone; Sodium Xylenesulfonate; Citric Acid Monohydrate; Fd&C Blue No. 1; Fd&C Red No. 4

Leader™ Dandruff Shampoo Everyday Clean
Anti-Dandruff

Drug Facts

Active ingredient

Pyrithione Zinc 1%

Purpose

Anti-dandruff

Use

helps prevent recurrence of flaking and itching associated with dandruff

Warnings

For external use only

When using this product

- do not get into eyes. If contact occurs, rinse eyes thoroughly with water

Stop use and ask a doctor if

- condition worsens or does not improve after regular use as directed

Keep out of reach of children. If swallowed, get medical help or contact a Poison Control Center (1-800-222-1222) right away.

Directions

- shake well
- wet hair
- massage onto scalp
- rinse
- repeat if desired
- for best results use at least twice a week or as directed by a doctor
- for maximum dandruff control, use every time you shampoo

Other information

store at room temperature

Inactive ingredients

water, sodium laureth sulfate, cocamide MEA, sodium lauryl sulfate, glycol distearate, dimethicone, fragrance, cetyl alcohol, guar hydroxypropyltrimonium chloride, magnesium sulfate, sodium benzoate, magnesium carbonate hydroxide, ammonium laureth sulfate, benzyl alcohol, sodium chloride, methylchloroisothiazolinone, methylisothiazolinone, sodium xylenesulfonate, citric acid, blue 1, red 4.

Questions or comments?

1-866-567-8600

DISTRIBUTED BY CARDINAL HEALTH
DUBLIN, OH 43017

PRINCIPAL DISPLAY PANEL - 369 mL Bottle Label

LEADER™

NDC 70000-0748-1

Dandruff
Shampoo

Pyrithione Zinc, 1%
Anti-Dandruff

Everyday
Clean

Basic Everyday
Cleaning for
Normal Hair

COMPARE TO
HEAD &
SHOULDERS®
active ingredient*

100% Money
Back Guarantee

12.5 FL OZ (369 mL)

05-3790B

Leader Dandruff Shampoo